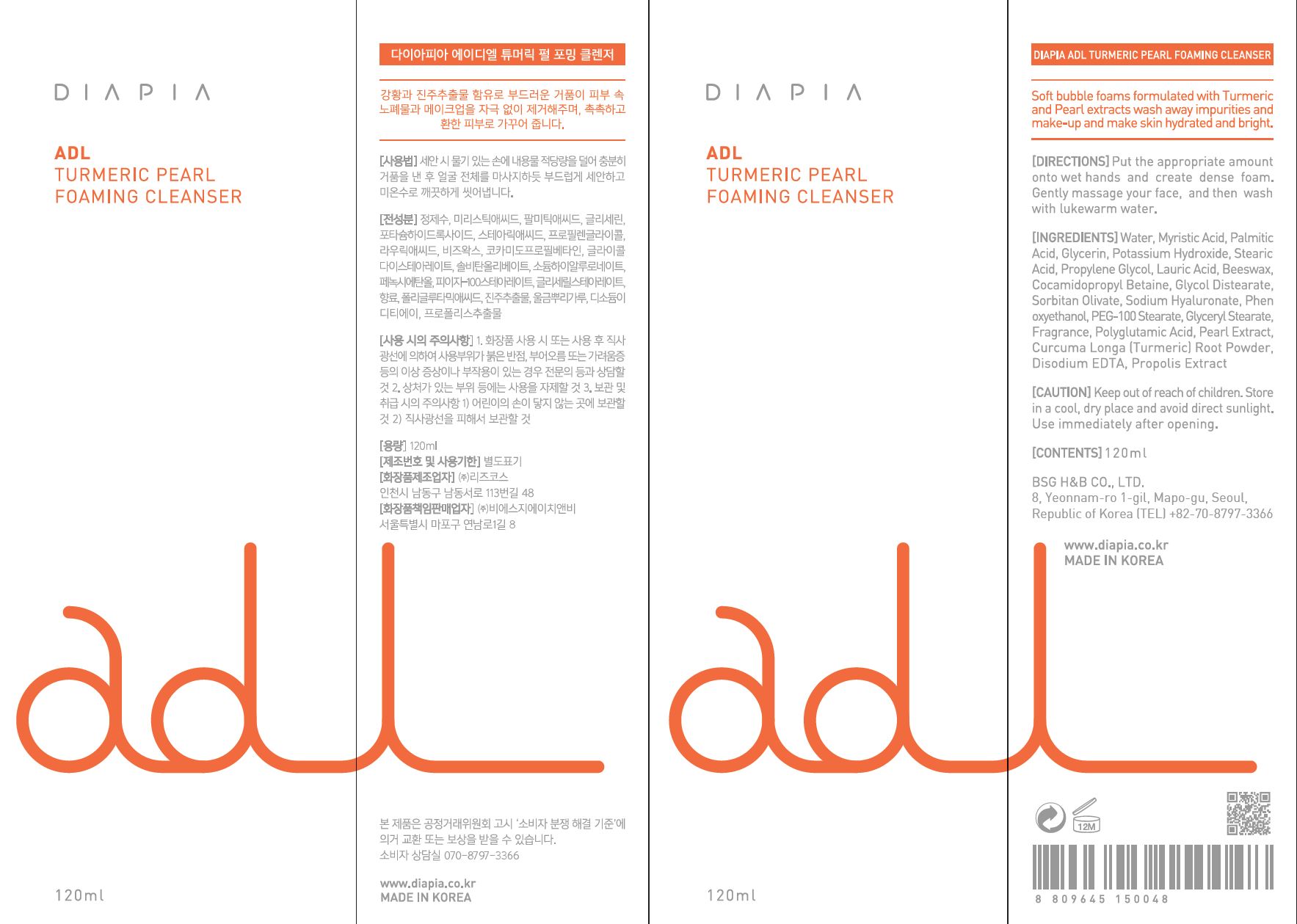 DRUG LABEL: DIAPIA ADL TURMERIC PEARL FOAMING CLEANSER
NDC: 71857-0014 | Form: LIQUID
Manufacturer: BSG H & B Co., Ltd.
Category: otc | Type: HUMAN OTC DRUG LABEL
Date: 20211210

ACTIVE INGREDIENTS: GLYCERIN 5 g/100 mL
INACTIVE INGREDIENTS: WATER

Drug Facts

ACTIVE INGREDIENT

glycerin

INACTIVE INGREDIENT

Myristic Acid
Palmitic Acid
Potassium Hydroxide
Stearic Acid
Propylene Glycol
Lauric Acid
Beeswax
Cocamidopropyl Betaine
Glycol Distearate
Sorbitan Olivate
Sodium Hyaluronate
Phenoxyethanol
PEG-100 Stearate
Glyceryl Stearate
Fragrance
Polyglutamic Acid
Pearl Extract
Curcuma Longa (Turmeric) Root
Powder
Disodium EDTA
Propolis Extract

PURPOSE

cleanse the skin

keep out of reach of the children

INDICATIONS AND USAGE

Put the appropriate amount onto wet hands and create dense foam. Gently massage your face, and then wash with lukewarm water.

WARNINGS

1.Keep out of reach of children.

2.Store in a cool, dry place and avoid direct sunlight.

3.If abnormal symptoms occur after use, stop use and consult with a skin specialist.

DOSAGE AND ADMINISTRATION

for external use only